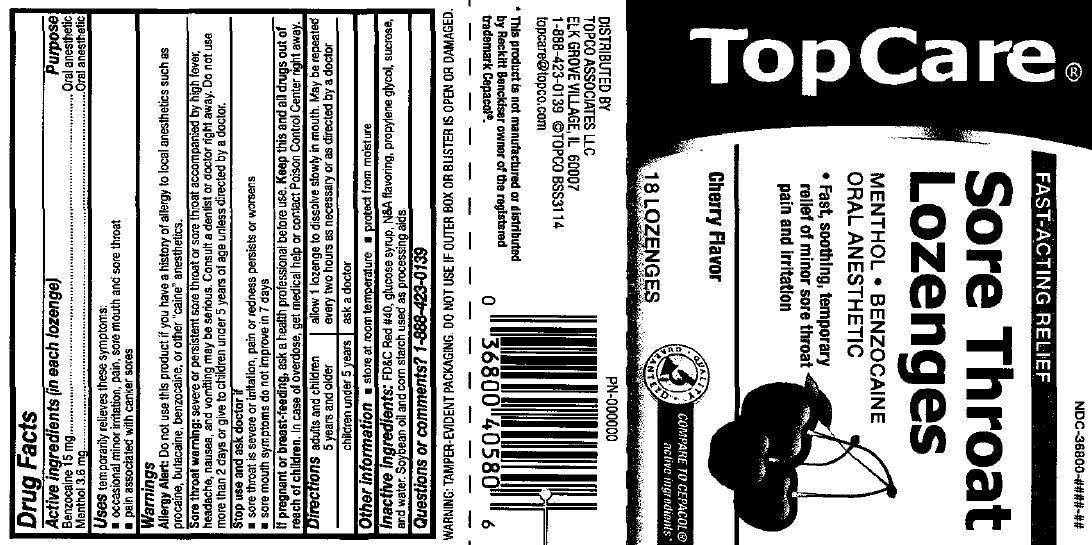 DRUG LABEL: TopCare Sore Throat Cherry Flavor
NDC: 36800-813 | Form: LOZENGE
Manufacturer: Topco Associates LLC
Category: otc | Type: HUMAN OTC DRUG LABEL
Date: 20140226

ACTIVE INGREDIENTS: BENZOCAINE 15 mg/1 1; MENTHOL 3.6 mg/1 1
INACTIVE INGREDIENTS: FD&C RED NO. 40; CORN SYRUP; PROPYLENE GLYCOL; SUCROSE; WATER; SOYBEAN OIL; STARCH, CORN

TopCare Cherry Sore Throat

ACTIVE INGREDIENT

Active ingredients (in each lozenge) | Purpose
Benzocaine 15 mg | Oral anesthetic
Menthol 3.6 mg | Oral anesthetic

Uses

temporarily relieves these symptoms:

- occasional minor irritation, pain, sore mouth and sore throat
- pain associated with canker sores

Warnings

Allergy Alert: Do not use this product if you have a history of allergy to local anesthetics such as procaine, butacaine, benzocaine, or any other "caine" anesthetics.

Sore throat warning:

Severe or persistent sore throat or sore throat accompanied by high fever, headache, rash, nausea, and vomiting may be serious. Consult a dentist or doctor right away. Do not use more than 2 days or administer to children under 5 years of age unless directed by a doctor.

Stop Use and ask a doctor if

- sore throat is severe or irritation, pain or redness persists or worsens
- sore mouth symptom do not improve in 7 days

PREGNANCY OR BREAST FEEDING

If pregnant or breast-feeding, ask a health professional before use.

KEEP OUT OF REACH OF CHILDREN

Keep this and all drugs out of the reach of children.

In case of overdose, get medical help or contact a Poison Control Center right away.

Directions

- adults and children 5 years of age and older: allow 1 lozenge to dissolve slowly in the mouth. May be repeated every 2 hours as needed or as directed by a doctor or dentist.
- children under 5 years: ask a doctor

Other information

- store at room temperature
- protect from moisture

Inactive ingredients

FD C Red 40, glucose syrup, N A Flavoring, propylene glycol, sucrose, and water. Soybean oil and corn starch used as processing aids.

Questions or comments?

1-888-423-0139

TopCare Sore Throat Lozenges Cherry Flavor 18 Count (36800-813-18)

TopCare

FAST-ACTING RELIEF

Sore Throat

Lozenges

MENTHOL • BENZOCAINE

ORAL ANESTHETIC

• Fast, soothing, temporary

relief of minor sore throat

pain and Irritation

Cherry Flavor

COMPARE TO CEPACOL

active ingredients

18 LOZENGES

DISTRIBUTED BY

TOPCO ASSOCIATES LLC

ELK GROVE VILLAGE, IL 60007

1-888-423-0139 ©TOPCO BSS3114

topcare@topco.com

This product is not manufactured or distributed

by Reckftt Bencldser owner af the registered

trademark Cepacol.